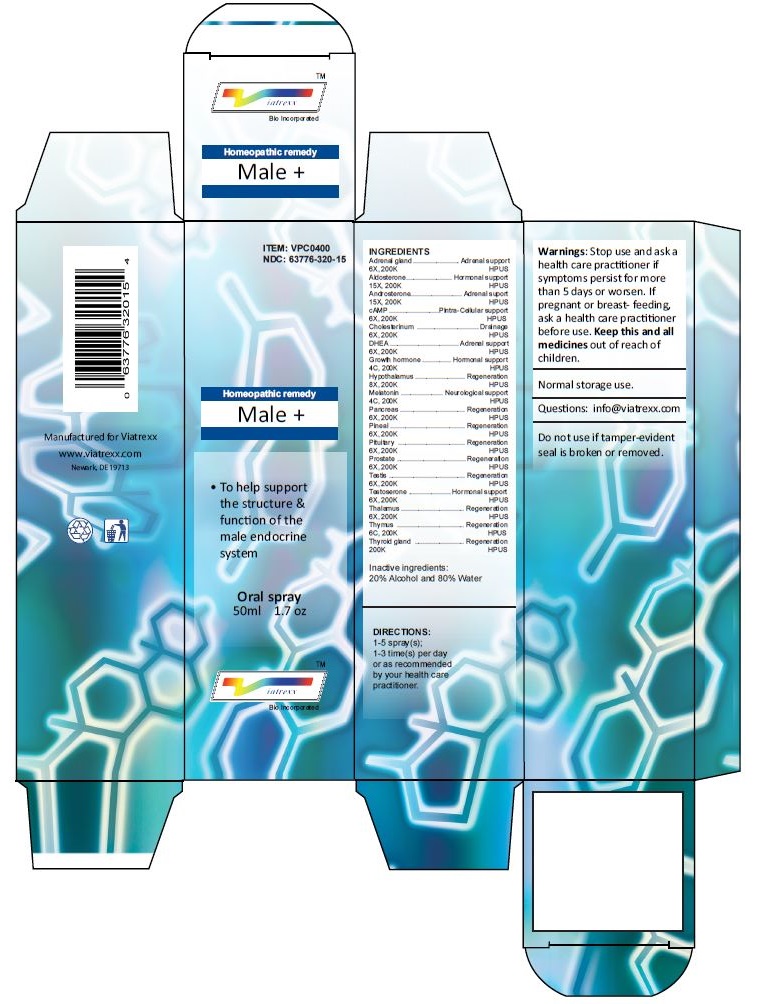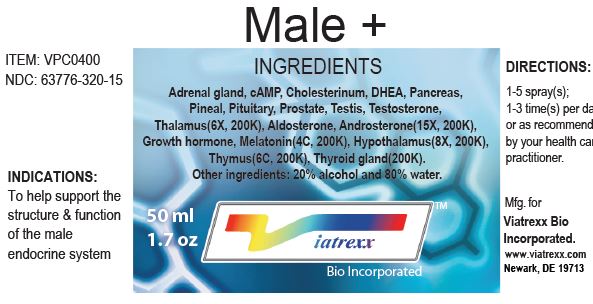 DRUG LABEL: Male plus
NDC: 63776-320 | Form: SPRAY
Manufacturer: VIATREXX BIO INCORPORATED
Category: homeopathic | Type: HUMAN OTC DRUG LABEL
Date: 20221130
DEA Schedule: CIII

ACTIVE INGREDIENTS: BOS TAURUS ADRENAL GLAND 200 [kp_C]/1 mL; SUS SCROFA ADRENAL GLAND 200 [kp_C]/1 mL; ALDOSTERONE 200 [kp_C]/1 mL; ANDROSTERONE 200 [kp_C]/1 mL; ADENOSINE CYCLIC PHOSPHATE 200 [kp_C]/1 mL; CHOLESTEROL 200 [kp_C]/1 mL; PRASTERONE 200 [kp_C]/1 mL; SOMATROPIN 200 [kp_C]/1 mL; BOS TAURUS HYPOTHALAMUS 200 [kp_C]/1 mL; SUS SCROFA HYPOTHALAMUS 200 [kp_C]/1 mL; MELATONIN 200 [kp_C]/1 mL; BOS TAURUS PANCREAS 200 [kp_C]/1 mL; SUS SCROFA PANCREAS 200 [kp_C]/1 mL; BOS TAURUS PINEAL GLAND 200 [kp_C]/1 mL; SUS SCROFA PINEAL GLAND 200 [kp_C]/1 mL; BOS TAURUS PITUITARY GLAND 200 [kp_C]/1 mL; SUS SCROFA PITUITARY GLAND 200 [kp_C]/1 mL; BOS TAURUS PROSTATE GLAND 200 [kp_C]/1 mL; SUS SCROFA PROSTATE 200 [kp_C]/1 mL; BOS TAURUS TESTICLE 200 [kp_C]/1 mL; SUS SCROFA TESTICLE 200 [kp_C]/1 mL; TESTOSTERONE 200 [kp_C]/1 mL; SUS SCROFA THALAMUS 200 [kp_C]/1 mL; BOS TAURUS THYMUS 200 [kp_C]/1 mL; SUS SCROFA THYMUS 200 [kp_C]/1 mL; THYROID, BOVINE 200 [kp_C]/1 mL; THYROID, PORCINE 200 [kp_C]/1 mL
INACTIVE INGREDIENTS: WATER; ALCOHOL

Male +

Active Ingredients

Adrenal gland (6X, 200K), Aldosterone (15X, 200K), Androsterone (15X, 200K), cAMP / Adenosinum cyclophosphoricum (6X, 200K), Cholesterinum (6X, 200K), DHEA (6X, 200K), Growth hormone (4C, 200K), Hypothalamus (8X, 200K), Melatonin (4C, 200K), Pancreas (6X, 200K), Pineal (6X, 200K), Pituitary (6X, 200K), Prostate (6X, 200K), Testis (6X, 200K), Testosterone (6X, 200K), Thalamus (6X, 200K), Thymus (6C, 200K), Thyroid gland (200K)

Purpose:

Adrenal gland | Adrenal support
Aldosterone | Hormonal support
Androsterone | Adrenal support
cAMP / Adenosinum cyclophosphoricum | Intra-Cellular support
Cholesterinum | Drainage
DHEA | Adrenal support
Growth hormone | Hormonal support
Hypothalamus | Regeneration
Melatonin | Neurological support
Pancreas | Regeneration
Pineal | Regeneration
Pituitary | Regeneration
Prostate | Regeneration
Testis | Regeneration
Testosterone | Hormonal support
Thalamus | Regeneration
Thymus | Regeneration
Thyroid gland | Regeneration

Uses

To help support the structure & function of the male endocrine system

Warnings

Stop use and ask a health care practitioner if symptoms persist for more than five days or worsen. If pregnant or breastfeeding, ask a health care practitioner before use.

Dosage

1-5 spray(s); 1-3 time(s) per day or as recommended by your health care practitioner.

KEEP OUT OF REACH OF CHILDREN

Keep this and all medicines out of reach of children.

Inactive Ingredients

20% Alcohol and 80% Water

Other Information

Normal storage use.
Do not use if tamper-evident seal is broken or removed.

Questions

info@viatrexx.com

Principal Display Panel

ITEM: VPC0400
NDC 63776-320-15
Homeopathic remedy
Male +
• To help support the structure & functin of the male endocrine system
Oral spray
50ml 1.7 oz
Viatrexx™ Bio Incorporated
Manufactured by Viatrexx
www.viatrexx.com
Newark, DE 19713

Male +
50 ml
1.7 oz
Viatrexx™ Bio Incorporated
ITEM: VPC0400
NDC: 63776-320-15
INDICATIONS:
To help support the structure & function of the male endocrine system
DIRECTIONS:
1-5 spray(s); 1-3 time(s) per day or as recommended by your health care practitioner.
Mfg. for
Viatrexx Bio Incorporated.
www.viatrexx.com
Newark, DE 19713